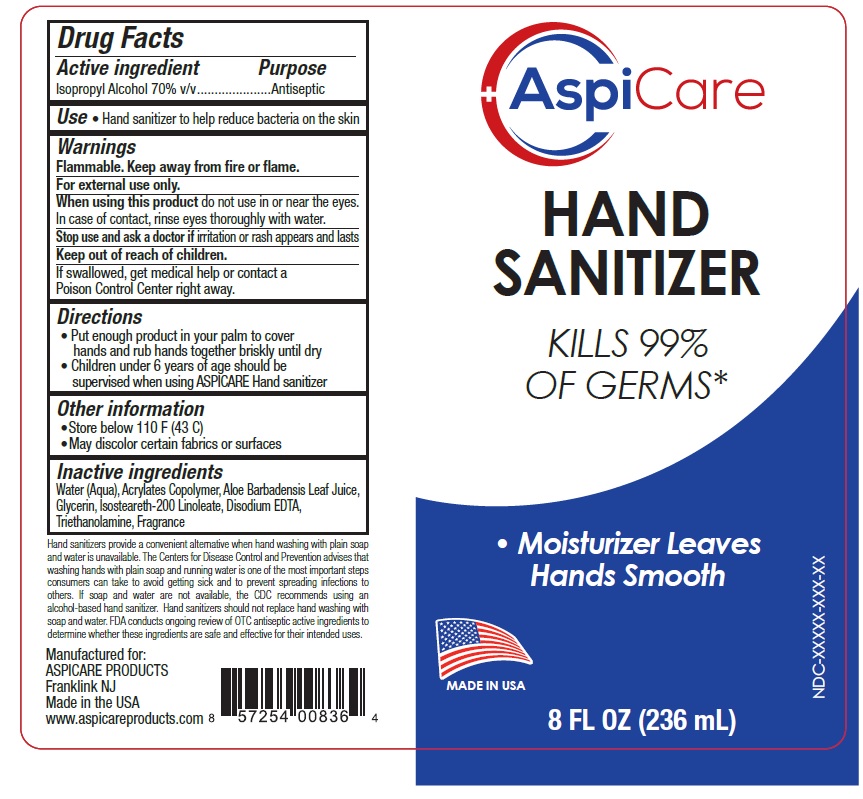 DRUG LABEL: AspiCare
NDC: 70735-071 | Form: SOLUTION
Manufacturer: American Private Label Products
Category: otc | Type: HUMAN OTC DRUG LABEL
Date: 20201204

ACTIVE INGREDIENTS: ISOPROPYL ALCOHOL 70 mL/100 mL
INACTIVE INGREDIENTS: WATER; BUTYL ACRYLATE/METHYL METHACRYLATE/METHACRYLIC ACID COPOLYMER (18000 MW); ALOE VERA LEAF; GLYCERIN; TROLAMINE; EDETATE DISODIUM

Active Ingredient

Isopropyl Alcohol 70% v/v.

Purpose

Antiseptic

Use

Hand Sanitizer to help reduce bacteria on the skin

Warnings

Flammable. Keep away from fire or flame. For external use only.

When using this product

do not use in or near the eyes. In case of contact, rinse eyes thoroughly with water.

Stop use and ask a doctor if

irritation or rash appears or lasts

Keep out of reach of children.

If swallowed, get medical help or contact a Poison Control Center right away.

Directions

- Put enough product in your palm to cover hands and rub hands together briskly until dry
- Children under 6 years of age should be supervised when using ASPICARE Hand sanitizer

Storage

- Store below 110°F (43°C)
- May discolor certain fabrics or surfaces

Inactive ingredients

Water (Aqua), Acrylates Copolymer, Aloe Barbadensis Leaf Juice, Glycerin, Isosteareth-200 Linoleate, Disodium EDTA, Fragrance, Triethanolamine

Other Information

Hand sanitizers provide a convenient alternative when hand washing with plain soap and water is unavailable. The Centers for Disease Control
and Prevention advises that washing hands with plain soap and running water is one of the most important steps consumers can take to avoid getting sick and to prevent spreading infections to others. If soap and water are not available, the CDC recommends using an alcohol-based hand sanitizer. Hand sanitizers should not replace hand washing with soap and water. FDA conducts ongoing review of OTC antiseptic active ingredients to determine whether these ingredients are safe and effective for their intended uses.

Principal Display Panel

NDC 70735-071-01

AspiCare

HAND SANITIZER

KILLS 99% OF GERMS*

Moisturizer Leaves Hands Smooth

MADE IN USA

1 FL OZ (30 mL)

NDC 70735-071-02

AspiCare

HAND SANITIZER

KILLS 99% OF GERMS*

Moisturizer Leaves Hands Smooth

MADE IN USA

2 FL OZ (60 mL)

NDC 70735-071-03

AspiCare

HAND SANITIZER

KILLS 99% OF GERMS*

Moisturizer Leaves Hands Smooth

MADE IN USA

3 FL OZ (89 mL)

NDC 70735-071-04

AspiCare

HAND SANITIZER

KILLS 99% OF GERMS*

Moisturizer Leaves Hands Smooth

MADE IN USA

4 FL OZ (118 mL)

NDC 70735-071-06

AspiCare

HAND SANITIZER

KILLS 99% OF GERMS*

Moisturizer Leaves Hands Smooth

MADE IN USA

6 FL OZ (177 mL)

NDC 70735-071-08

AspiCare

HAND SANITIZER

KILLS 99% OF GERMS*

Moisturizer Leaves Hands Smooth

MADE IN USA

8 FL OZ (236 mL)

NDC 70735-071-16

AspiCare

HAND SANITIZER

KILLS 99% OF GERMS*

Moisturizer Leaves Hands Smooth

MADE IN USA

16 FL OZ (473 mL)

NDC 70735-071-32

AspiCare

HAND SANITIZER

KILLS 99% OF GERMS*

Moisturizer Leaves Hands Smooth

MADE IN USA

32 FL OZ (946 mL)